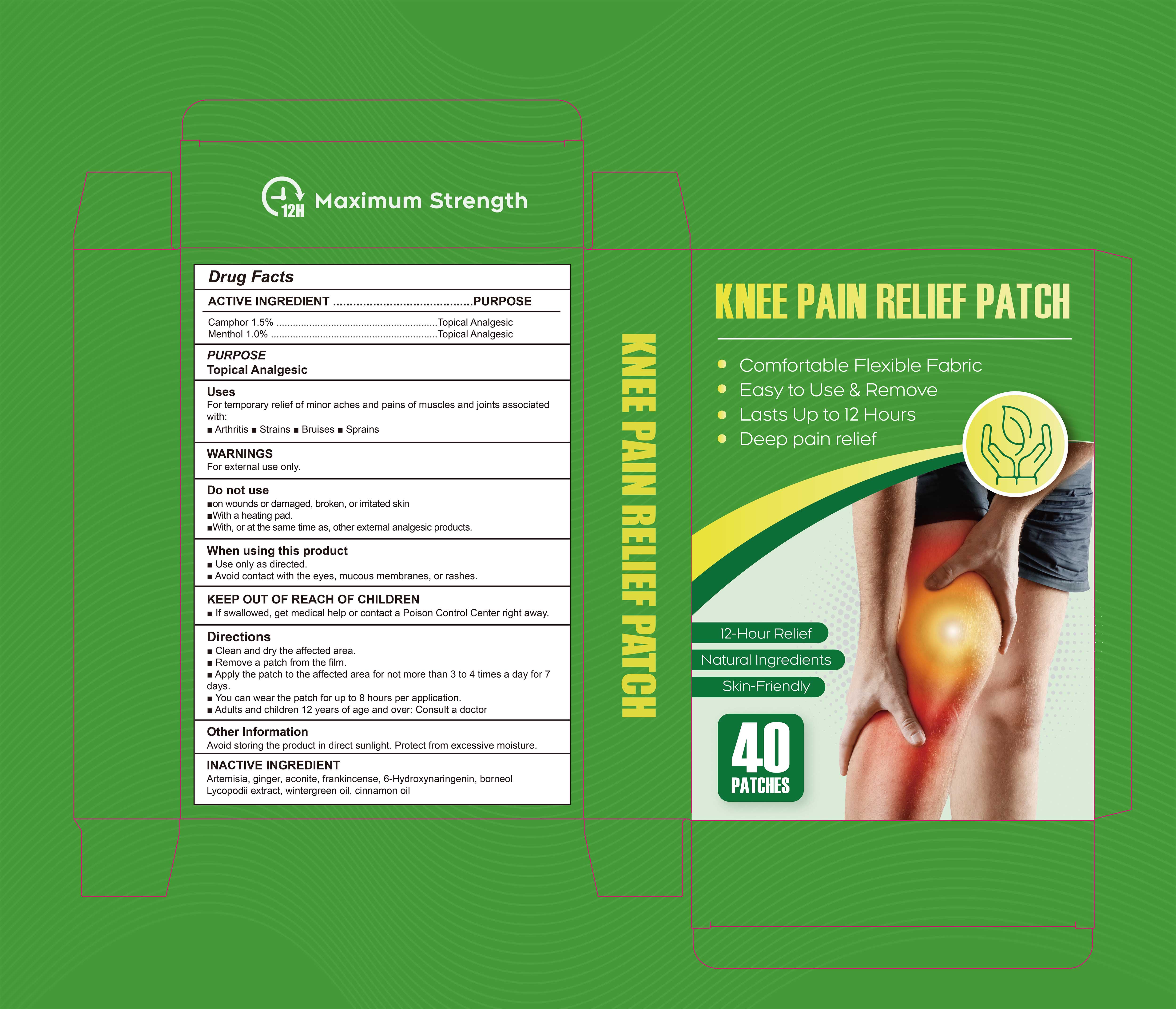 DRUG LABEL: KNEE PAIN RELIRF Patch
NDC: 85839-010 | Form: PATCH
Manufacturer: Shenzhen Finona Information Technology Co., Ltd
Category: otc | Type: HUMAN OTC DRUG LABEL
Date: 20250901

ACTIVE INGREDIENTS: CAMPHOR (SYNTHETIC) 0.015 g/1 1; MENTHOL 0.01 g/1 1
INACTIVE INGREDIENTS: BORNEOL; CARTHAMUS TINCTORIUS WHOLE; ARTEMISIA ABSINTHIUM OIL; LYCOPODIUM JAPONICUM WHOLE; FRANKINCENSE; GINGER; ACONITUM NAPELLUS ROOT; METHYL SALICYLATE; CINNAMON OIL

85839-010 KNEE PAIN RELIRF PATCH

ACTIVE INGREDIENT

Camphor 1.5%
Menthol 1%

PURPOSE

Topical Analgesic

INDICATIONS AND USAGE

For temporary relief of minor aches and pains of muscles and joints associated
with:
Arthritis. Strains. Bruises. Sprains

WARNINGS

For external use only.

DO NOT USE

on wounds or damaged, broken, or irritated skin
With a heating pad.
With, or at the same time as, other external analgesic products,

WHEN USING

Use only as directed.
Avoid contact with the eyes, mucous membranes, or rashes

KEEP OUT OF REACH OF CHILDREN

If swallowed, get medical help or contact a Poison Control Center right away.

DOSAGE AND ADMINISTRATION

Clean and dry the affected area.
Remove a patch from the film.
Apply the patch to the affected area for not more than 3 to 4 times a day for 7 days.
You can wear the patch for up to 8 hours per application.
Adults and children 12 years of age and over: Consult a doctor

INACTIVE INGREDIENT

Artemisia, ginger, aconite, frankincense, 6-Hydroxynaringenin, borneolLycopodii extract, wintergreen oil, cinnamon oil